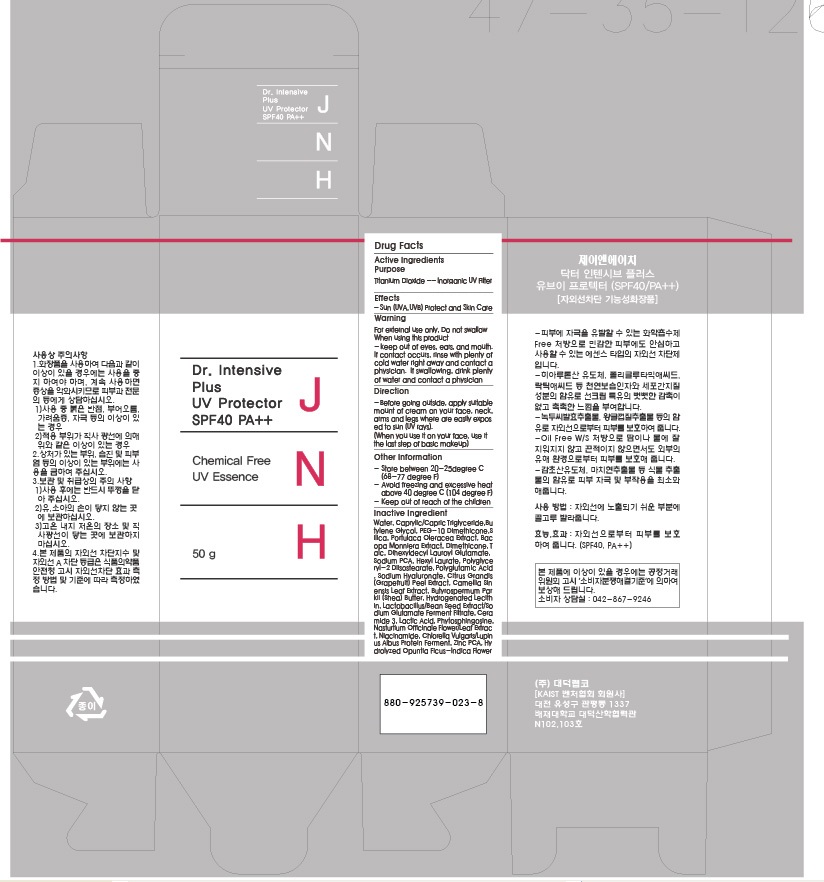 DRUG LABEL: JNH Dr. Intensive Plus UV Protector
NDC: 53010-1001 | Form: CREAM
Manufacturer: Daeduck Lab Co., Ltd
Category: otc | Type: HUMAN OTC DRUG LABEL
Date: 20120824

ACTIVE INGREDIENTS: TITANIUM DIOXIDE 1.5 g/50 g
INACTIVE INGREDIENTS: BUTYLENE GLYCOL; PEG-10 DIMETHICONE (600 CST); SILICON DIOXIDE; PORTULACA OLERACEA WHOLE; BACOPA MONNIERA LEAF; DIMETHICONE; TALC; SODIUM PYRROLIDONE CARBOXYLATE; ETHYLHEXYL LAURATE; GLUTAMIC ACID; HYALURONATE SODIUM; CITRUS MAXIMA FRUIT RIND; GREEN TEA LEAF; SHEA BUTTER; HYDROGENATED SOYBEAN LECITHIN; CERAMIDE 3; LACTIC ACID; PHYTOSPHINGOSINE; NASTURTIUM OFFICINALE WHOLE; NIACINAMIDE; CHLORELLA VULGARIS; LUPINUS ALBUS SEED; ZINC PIDOLATE; OPUNTIA FICUS-INDICA FLOWER

Drug Facts

ACTIVE INGREDIENT

titanium dioxide

INACTIVE INGREDIENT

- Water - Caprylic/Capric Triglyceride - Butylene Glycol - PEG-10 Dimethicone - Silica - Portulaca Oleracea Extract - Bacopa Monniera Extract - Dimethicone - Talc - Dihexyldecyl Lauroyl Glutamate - Sodium PCA - Hexyl Laurate - Polyglyceryl-2 Diisostearate
- Polyglutamic Acid - Sodium Hyaluronate - Citrus Grandis (Grapefruit) Peel Extract - Camellia Sinensis Leaf Extract - Butyrospermum Parkii (Shea) Butter - Hydrogenated Lecithin - Lactobacillus/Bean Seed Extract/Sodium Glutamate Ferment Filtrate - Ceramide 3
- Lactic Acid – Phytosphingosine - Nasturtium Officinale Flower/Leaf Extract - Niacinamide - Chlorella Vulgaris/Lupinus Albus Protein Ferment - Zinc PCA - Hydrolyzed Opuntia Ficus-Indica Flower

PURPOSE

sun protect and skin care

keep out of reach of the children

INDICATIONS AND USAGE

- Before going outside, apply suitable mount of cream on your face, neck, arms and legs where are easily exposed to sun (UV rays). (When you use it on your face, use it the last step of basic makeup)

When using this product
- keep out of eyes, ears, and mouth. If contact occurs, rinse with plenty of cold water right away and contact a physician. If swallowing, drink plenty of water and contact a physician

DOSAGE AND ADMINISTRATION

for external use only